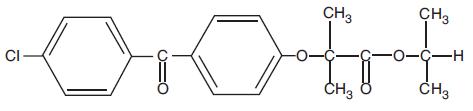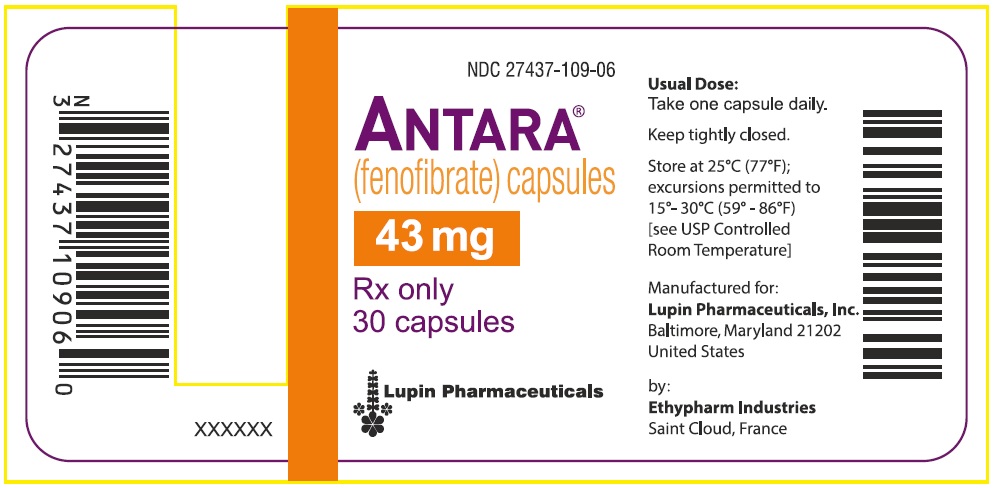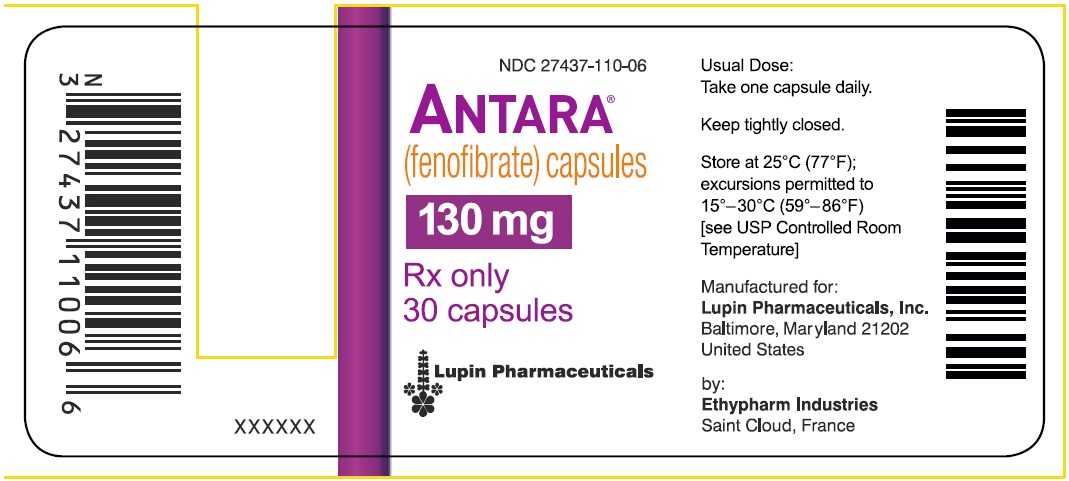 DRUG LABEL: ANTARA
NDC: 27437-109 | Form: CAPSULE
Manufacturer: Lupin Pharmaceuticals, Inc.
Category: prescription | Type: HUMAN PRESCRIPTION DRUG LABEL
Date: 20251001

ACTIVE INGREDIENTS: FENOFIBRATE 43 mg/1 1
INACTIVE INGREDIENTS: D&C YELLOW NO. 10; FD&C BLUE NO. 2; FERRIC OXIDE YELLOW; GELATIN; HYPROMELLOSES; SODIUM LAURYL SULFATE; SUCROSE; DIMETHICONE; SULFUR DIOXIDE; LECITHIN, SOYBEAN; SHELLAC; TALC; TITANIUM DIOXIDE; FERROSOFERRIC OXIDE

HIGHLIGHTS OF PRESCRIBING INFORMATION

These highlights do not include all the information needed to use ANTARA safely and effectively. See full prescribing information for ANTARA.
ANTARA (fenofibrate) capsules, for oral use
Initial U.S. Approval: 1993

1 INDICATIONS AND USAGE

Antara is a peroxisome proliferator-activated receptor (PPAR) alpha agonist indicated as an adjunct to diet:

- to reduce triglyceride (TG) levels in adults with severe hypertriglyceridemia (TG greater than or equal to 500 mg/dL) (1).
- to reduce elevated low-density lipoprotein cholesterol (LDL-C) in adults with primary hyperlipidemia when use of recommended LDL-C lowering therapy is not possible (1).

Limitations of Use:

- Markedly elevated levels of serum TG (e.g., > 2,000 mg/dL) may increase the risk of developing pancreatitis. The effect of fenofibrate therapy on reducing this risk has not been determined (1).
- Fenofibrate did not reduce coronary heart disease morbidity and mortality in two large, randomized controlled trials of patients with type 2 diabetes mellitus (1).

2 DOSAGE AND ADMINISTRATION

- Severe hypertriglyceridemia: 43 mg to 130 mg orally once daily; the dosage should be adjusted according to patient response (2.2)
- Primary hyperlipidemia: 130 mg orally once daily (2.2).
- Administer as a single dose, at any time of day, with or without food (2.2).
- Assess TG when clinically appropriate, as early as 4 to 8 weeks after initiating Antara. Discontinue Antara in patients who do not have an adequate response after 2 months of treatment (2.2).
- Renal impairment: Initial dosage of 43 mg orally once daily (2.3).
- Geriatric patients: Select the dosage on the basis of renal function (2.4).

3 DOSAGE FORMS AND STRENGTHS

- Capsules: 43 mg and 130 mg (3).

4 CONTRAINDICATIONS

- Severe renal impairment, including those with end-stage renal disease (ESRD) and those receiving dialysis (4)
- Active liver disease, including those with unexplained persistent liver function abnormalities (4)
- Pre-existing gallbladder disease (4)
- Hypersensitivity to fenofibrate fenofibric acid, or any of the excipients in Antara (4)

5 WARNINGS AND PRECAUTIONS

- Hepatotoxicity: Serious drug-induced liver injury, including liver transplantation and death, has been reported with fenofibrates, including Antara. Monitor patient's liver function, including serum ALT, AST, and total bilirubin, at baseline and periodically for the duration of therapy. Discontinue if signs or symptoms of liver injury develop or if elevated enzyme levels persist (5.2).
- Myopathy and Rhabdomyolysis: Have been reported in patients taking fenofibrates. Risks are increased during co-administration with a statin, in geriatric patients and in patients with renal impairment, or hypothyroidism. Discontinue Antara if markedly elevated CK levels occur or if myopathy is either diagnosed or suspected. Temporarily discontinue Antara in patients experiencing an acute or serious condition at high risk of developing renal failure secondary to rhabdomyolysis. Inform patients of the risk of myopathy and rhabdomyolysis when starting or increasing the Antara dosage. Instruct patients to promptly report any unexplained muscle pain, tenderness, or weakness, particularly if accompanied by malaise or fever (5.3).
- Increases in Serum creatinine: Monitor renal function in patients with renal impairment taking Antara. Consider monitoring renal function in patients at risk for renal impairment (5.4).
- Cholelithiasis: Fenofibrate may increase cholesterol excretion into the bile, leading to cholelithiasis. If cholelithiasis is suspected, gallbladder studies are indicated (5.5).
- Hypersensitivity Reactions: Acute hypersensitivity reactions, including anaphylaxis and angioedema, and delayed hypersensitivity reactions, including severe cutaneous adverse drug reactions have been reported postmarketing. Some cases were life-threatening and required emergency treatment. Discontinue Antara and treat appropriately if reactions occur (5.9).

6 ADVERSE REACTIONS

Adverse reactions (> 2% and greater than placebo) abnormal liver tests, increased AST, increased ALT, increased CPK, and rhinitis (6.1).

To report SUSPECTED ADVERSE REACTIONS, contact Lupin Pharmaceuticals, Inc. at 1-800-399-2561 or FDA at 1-800-FDA-1088 or www.fda.gov/medwatch.

7 DRUG INTERACTIONS

- Consider if the benefit of concomitant use of statins or colchicine outweighs the increased risk of myopathy and rhabdomyolysis. Monitor patients for signs and symptoms of myopathy (7).
- Exercise caution in concomitant treatment with coumarin anticoagulants.
- Reduce the dosage of coumarin to maintain the PT/INR at the desired level to prevent bleeding complications (7).
- Consider the benefits and risks of concomitant use with immunosuppressants and other potentially nephrotoxic agents. Use the lowest effective dosage and monitor renal function (7).
- Administer Antara at least 1 hour before or 4 to 6 hours after a bile acid resin to avoid impeding its absorption (7).

FULL PRESCRIBING INFORMATION

1 INDICATIONS AND USAGE

Antara is indicated as adjunctive therapy to diet:

- to reduce triglyceride (TG) levels in adults with severe hypertriglyceridemia (TG greater than or equal to 500 mg/dL).
- to reduce elevated low-density lipoprotein cholesterol (LDL-C) in adults with primary hyperlipidemia when use of recommended LDL-C lowering therapy is not possible.

Limitations of Use

- Markedly elevated levels of serum TG (e.g., > 2,000 mg/dL) may increase the risk of developing pancreatitis. The effect of fenofibrate therapy on reducing this risk has not been determined [see Warnings and Precautions (5.7)].
- Fenofibrate did not reduce coronary heart disease morbidity and mortality in two large, randomized controlled trials of patients with type 2 diabetes mellitus [see Warnings and Precautions (5.1) and Clinical Studies (14.4)].

2 DOSAGE AND ADMINISTRATION

2.1 Prior to Initiation of Antara

- Assess lipid levels before initiating therapy. Identify other causes (e.g., diabetes mellitus, hypothyroidism, or medications) of high TG levels and manage as appropriate.
- Patients should be placed on an appropriate lipid-lowering diet before receiving Antara and should continue this diet during treatment with Antara.
- In patients with diabetes and fasting chylomicronemia, improve glycemic control prior to considering starting Antara.

2.2 Recommended Dosage and Administration

• Severe hypertriglyceridemia:

○ The recommended dosage of Antara is 43 mg or 130 mg orally once daily.

○ Dosage should be individualized according to patient response, and should be adjusted if necessary following repeat lipid determinations at 4 to 8 week intervals.

• Primary hyperlipidemia:

○ The recommended dosage of Antara is 130 mg orally once daily.

• Administer Antara as a single dose at any time of day, with or without food.

• Advise patients to swallow Antara capsules whole. Do not crush, break, dissolve, or chew capsules.

• Assess TG when clinically appropriate, as early as 4 to 8 weeks after initiating Antara. Discontinue Antara in patients who do not have an adequate response after 2 months of treatment.

• If a dose is missed, advise patients not to take an extra dose. Resume treatment with the next dose.

• Advise patients to take Antara at least 1 hour before or 4 hours to 6 hours after a bile acid binding resin to avoid impeding its absorption.

2.3 Recommended Dosage in Patients with Renal Impairment

- Assess renal function prior to initiation of Antara and periodically thereafter [see Warnings and Precautions (5.4)].
- Treatment with Antara should be initiated at a dosage of 43 mg orally once daily in patients with mild to moderately impaired renal function (eGFR 30 to <60 mL/min/1.73m^2), and increased only after evaluation of the effects on renal function and TG levels at this dosage.
- Antara is contraindicated in patients with severe renal impairment (eGFR <30 mL/min/1.73m^2), including those with end-stage renal disease (ESRD) and those receiving dialysis [see Use in Specific Populations (8.6)and Clinical Pharmacology (12.3)].

2.4 Recommended Dosage in Geriatric Patients

Dosage selection for geriatric patients should be made on the basis of renal function [see Use in Specific Populations (8.6) and Clinical Pharmacology (12.3)]

3 DOSAGE FORMS AND STRENGTHS

Antara Capsules:

- 43 mg; capsules, imprinted with "43" and a segmented band, on the light green cap and "ANTARA" and "LUPIN" on the white to off-white body.
- 130 mg; capsules, imprinted with "130" and a segmented band, on the dark green cap and "ANTARA" and "LUPIN" on the white body.

4 CONTRAINDICATIONS

Antara is contraindicated in patients with:

- Severe renal impairment, including those with end-stage renal disease (ESRD) and those receiving dialysis [see Clinical Pharmacology (12.3)].
- Active liver disease, including those with unexplained persistent liver function abnormalities[see Warnings and Precautions (5.2)].
- Pre-existing gallbladder disease [see Warnings and Precautions (5.5)].
- Hypersensitivity to fenofibrate, fenofibric acid, or any of the excipients in Antara. Serious hypersensitivity reactions including anaphylaxis and angioedema have been reported with fenofibrate [see Warnings and Precautions (5.9)].

5 WARNINGS AND PRECAUTIONS

5.1 Mortality and Coronary Heart Disease Morbidity

Fenofibrate did not reduce cardiovascular disease morbidity or mortality in two large, randomized controlled trials of patients with type 2 diabetes mellitus [see Clinical Studies (14.4)].

Because of chemical, pharmacological, and clinical similarities between fenofibrates, including Antara; pemafibrate; clofibrate; and gemfibrozil; the findings in 5 large randomized, placebo-controlled clinical trials with these other fibrate drugs may also apply to Antara.

Pemafibrate did not reduce cardiovascular disease morbidity or mortality in a large, randomized, placebo-controlled trial of patients with type 2 diabetes mellitus on background statin therapy [see Clinical Studies (14.4)].

In the Coronary Drug Project, a large trial conducted from 1965 to 1985 in men post myocardial infarction, there was no difference in mortality or nonfatal myocardial infarction between the clofibrate group and the placebo group after 5 years of treatment (NCT00000482).

In a trial conducted by the World Health Organization (WHO) from 1965 to 1976, men without known coronary artery disease were treated with placebo or clofibrate for 5 years and followed for an additional 1 year. There was a statistically significant, higher age-adjusted all-cause mortality in the clofibrate group compared with the placebo group (5.70% vs. 3.96%, p≤0.01). Excess mortality was due to a 33% increase in non-cardiovascular causes, including malignancy, post-cholecystectomy complications, and pancreatitis.

The Helsinki Heart Study, conducted from 1982 to 1987, was a large (n=4,081) trial of middle-aged men without a history of coronary artery disease. Subjects received either placebo or gemfibrozil for 5 years, with a 3.5-year open extension afterward. Total mortality was numerically but not statistically higher in the gemfibrozil randomization group versus placebo [95% confidence interval (CI) of the hazard ratio (HR) 0.91 to 1.64].

A secondary prevention component of the Helsinki Heart Study treated middle-aged men with gemfibrozil or placebo for 5 years. The HR for cardiac deaths was 2.2, 95% CI, 0.94 to 5.05.

5.2 Hepatotoxicity

Serious drug-induced liver injury (DILI), including liver transplantation and death, has been reported with postmarketing use of fenofibrates, including Antara. DILI has been reported within the first few weeks of treatment or after several months of therapy and in some cases has reversed with discontinuation of Antara treatment. Patients with DILI have experienced signs and symptoms including dark urine, abnormal stool, jaundice, malaise, abdominal pain, myalgia, weight loss, pruritus, and nausea. Many patients had concurrent elevations of total bilirubin, serum alanine transaminase (ALT), and aspartate transaminase (AST). DILI has been characterized as hepatocellular, chronic active, and cholestatic hepatitis, and cirrhosis has occurred in association with chronic active hepatitis.

In clinical trials, an intermediate daily dosage or the maximum recommended daily dosage of fenofibrate have been associated with increases in serum AST or ALT. The incidence of increases in transaminases may be dose related [see Adverse Reactions (6.1)].

Antara is contraindicated in patients with active liver disease, including those with unexplained persistent liver function abnormalities. Monitor patient's liver function, including serum ALT, AST, and total bilirubin, at baseline and periodically for the duration of therapy with Antara. Discontinue Antara if signs or symptoms of liver injury develop or if elevated enzyme levels persist (ALT or AST > 3 times the upper limit of normal, or if accompanied by elevation of bilirubin). Do not restart Antara in these patients if there is no alternative explanation for the liver injury.

5.3 Myopathy and Rhabdomyolysis

Antara may cause myopathy [muscle pain, tenderness, or weakness associated with elevated creatine kinase (CK)] and rhabdomyolysis.

Risk Factors for Myopathy

Risk factors for myopathy include age 65 years or older, uncontrolled hypothyroidism, renal impairment, and concomitant use with certain other drugs [see Drug Interactions (7) and Use in Specific Populations (8.6)].

Steps to Prevent or Reduce the Risk of Myopathy and Rhabdomyolysis

Data from observational studies indicate that the risk for rhabdomyolysis is increased when fibrates, including fenofibrates, are co-administered with a statin. Avoid concomitant use unless the benefit of further alterations in TG levels is likely to outweigh the increased risk of this drug combination [see Drug Interactions (7), Clinical Pharmacology (12.3), and Clinical Studies (14.4)].

Cases of myopathy, including rhabdomyolysis, have been reported with fenofibrates, including Antara, co-administered with colchicine. Consider whether the benefit of using colchicine concomitantly with Antara outweighs the increased risk of myopathy. [see Drug Interactions (7)].

Discontinue Antara if markedly elevated CK levels occur or if myopathy is either diagnosed or suspected. Muscle symptoms and CK elevations may resolve if Antara is discontinued. Temporarily discontinue Antara in patients experiencing an acute or serious condition at high risk of developing renal failure secondary to rhabdomyolysis (e.g., sepsis; shock; severe hypovolemia; major surgery; trauma; severe metabolic, endocrine, or electrolyte disorders; or uncontrolled epilepsy).

Inform patients of the risk of myopathy and rhabdomyolysis when starting or increasing the Antara dosage. Instruct patients to promptly report any unexplained muscle pain, tenderness or weakness, particularly if accompanied by malaise or fever.

5.4 Increases in Serum Creatinine

Increases in serum creatinine have been reported in patients receiving fenofibrates. These increases tend to return to baseline following discontinuation of Antara. The clinical significance of this finding is unknown. Monitor renal function in patients with renal impairment taking Antara. Renal monitoring should also be considered for patients taking Antara at risk for renal insufficiency, such as geriatric patients and patients with diabetes. Antara is contraindicated in patients with severe renal impairment, including those with end-stage renal disease (ESRD) and those receiving dialysis [see Dosage and Administration (2.3), Use in Specific Populations (8.6), and Clinical Pharmacology (12.3)].

5.5 Cholelithiasis

Fenofibrate may increase cholesterol excretion into the bile, leading to cholelithiasis. If cholelithiasis is suspected, gallbladder studies are indicated. Antara therapy should be discontinued if gallstones are found. Antara is contraindicated in patients with pre-existing gallbladder disease.

5.6 Increased Bleeding Risk with Coumarin Anticoagulants

Exercise caution when co-administering anticoagulants with Antara because of the potentiation of coumarin-type anticoagulant effects in prolonging the prothrombin time/International Normalized Ratio (PT/INR). To prevent bleeding complications, monitor the PT/INR frequently and adjust the dosage of the anticoagulant until the PT/INR has stabilized [see Drug Interactions (7)].

5.7 Pancreatitis

Pancreatitis has been reported in patients taking fenofibrates. This occurrence may represent a failure of efficacy in patients with severe hypertriglyceridemia, a direct drug effect, or a secondary phenomenon mediated through biliary tract stone or sludge formation with obstruction of the common bile duct.

5.8 Hematologic Changes

Mild to moderate hemoglobin, hematocrit, and white blood cell decreases have been observed in patients following initiation of therapy with fenofibrates. However, these levels stabilize during long-term administration. Thrombocytopenia and agranulocytosis have been reported in individuals treated with Antara. Periodic monitoring of red and white blood cell counts is recommended during the first 12 months of Antara administration.

5.9 Hypersensitivity Reactions

Acute Hypersensitivity

Anaphylaxis and angioedema have been reported with postmarketing use of fenofibrates. In some cases, reactions were life-threatening and required emergency treatment. If a patient develops signs or symptoms of an acute hypersensitivity reaction, advise them to seek immediate medical attention and discontinue Antara. Antara is contraindicated in patients with a hypersensitivity to fenofibrate, fenofibric acid, or any of the ingredients in Antara.

Delayed Hypersensitivity

Severe cutaneous adverse drug reactions (SCAR), including Stevens-Johnson syndrome, Toxic Epidermal Necrolysis, and Drug Reaction with Eosinophilia and Systemic Symptoms (DRESS), have been reported with post-marketing use of fenofibrates, occurring days to weeks after treatment initiation. The cases of DRESS were associated with cutaneous reactions (such as rash or exfoliative dermatitis) and a combination of eosinophilia, fever, systemic organ involvement (renal, hepatic, or respiratory). Discontinue Antara and treat patients appropriately if SCAR is suspected.

5.10 Venothromboembolic Disease

In the Fenofibrate Intervention and Event Lowering in Diabetes (FIELD) trial, pulmonary embolus (PE) and deep vein thrombosis (DVT) were observed at higher rates in the fenofibrate than the placebo-treated group. Of 9,795 patients enrolled in FIELD, there were 4,900 in the placebo group and 4,895 in the fenofibrate group. For DVT, there were 48 events (1%) in the placebo group and 67 (1.4%) in the fenofibrate group (p = 0.074); and for PE, there were 32 (0.7%) events in the placebo group and 53 (1.1%) in the fenofibrate group (p = 0.022).

In the Coronary Drug Project, a higher proportion of the clofibrate group experienced definite or suspected fatal or nonfatal pulmonary embolism or thrombophlebitis than the placebo group (5.2% vs. 3.3% at five years; p < 0.01).

In the cardiovascular outcome trial with pemafibrate, pulmonary embolism was reported for 37 (0.7%) subjects in the pemafibrate group and 16 (0.3%) subjects in the placebo group. Deep vein thrombosis was reported for 36 (0.7%) subjects in the pemafibrate group and 13 (0.2%) subjects in the placebo group.

5.11 Paradoxical Decrease in HDL Cholesterol Levels

There have been postmarketing and clinical trial reports of severe decreases in high-density lipoprotein cholesterol (HDL-C) levels (as low as 2 mg/dL) occurring in patients with and without diabetes initiated on fibrate therapy, including fenofibrate. The decrease in HDL-C is mirrored by a decrease in apolipoprotein A1. This decrease has been reported to occur within 2 weeks to years after initiation of fibrate therapy. The HDL-C levels remain depressed until fibrate therapy has been withdrawn; the response to withdrawal of fibrate therapy is rapid and sustained. The clinical significance of this decrease in HDL-C is unknown. Check HDL-C levels within the first few months after initiation of Antara. If a severely depressed HDL-C level is detected, discontinue Antara and monitor HDL-C until it has returned to baseline. Antara should not be re-initiated.

6 ADVERSE REACTIONS

The following serious adverse reactions are described below and elsewhere in the labeling:

- Mortality and coronary heart disease morbidity [see Warnings and Precautions (5.1)]
- Hepatoxicity [see Warnings and Precautions (5.2)]
- Myopathy and Rhabdomyolysis [see Warnings and Precautions (5.3)]
- Increases in Serum Creatinine [see Warnings and Precautions (5.4)]
- Cholelithiasis [see Warnings and Precautions (5.5)]
- Increased Bleeding Risk with Coumarin Anticoagulants [see Warnings and Precautions (5.6)]
- Pancreatitis [see Warnings and Precautions (5.7)]
- Hematologic Changes [see Warnings and Precautions (5.8)]
- Hypersensitivity reactions [see Warnings and Precautions (5.9)]
- Venothromboembolic disease [see Warnings and Precautions (5.10)]
- Paradoxical Decreases in HDL Cholesterol Levels [see Warnings and Precautions (5.11)]

6.1 Clinical Trials Experience

Because clinical trials are conducted under widely varying conditions, adverse reaction rates observed in the clinical trials of a drug cannot be directly compared to rates in the clinical trials of another drug and may not reflect the rates observed in clinical practice.

The safety of Antara has been established in adults with hypertriglyceridemia or primary hyperlipidemia based on adequate and well-controlled trials of other formulations of fenofibrate, referenced below as "fenofibrate" [see Clinical Studies (14)]. Dosages of fenofibrate used in these trials were comparable to Antara 90 mg per day [see Clinical Pharmacology (12.3)].

Adverse reactions reported by 2% or more of patients treated with fenofibrate (and greater than placebo) during the double-blind, placebo-controlled trials are listed in Table 1 below. Adverse reactions led to discontinuation of treatment in 5% of patients treated with fenofibrate and in 3% treated with placebo. Increases in liver function tests were the most frequent events, causing discontinuation of fenofibrate treatment in 1.6% of patients in double-blind trials.

Table 1: Adverse Reactions Reported by 2% or More of Patients Treated with Fenofibrate and Greater than Placebo During the Double-Blind, Placebo-Controlled Trials
Adverse Reaction | Placebo (N = 365) | Fenofibrate (N = 439)
Abnormal Liver Tests | 1% | 8%
Abdominal Pain | 4% | 5%
Increased ALT | 2% | 3%
Increased AST | 1% | 3%
Increased Creatine Phosphokinase | 1% | 3%
Constipation | 1% | 2%
Rhinitis | 1% | 2%

Other Adverse Reactions

Urticaria

Urticaria was seen in 1.1% vs. 0% and rash in 1.4% vs. 0.8% of fenofibrate and placebo patients respectively in controlled trials.

Increases in Liver Enzymes

In a pooled analysis of 10 placebo-controlled trials, increases to >3 times the upper limit of normal in ALT occurred in 5.3% of patients taking either an intermediate or the maximum recommended daily dosage of fenofibrate versus 1.1% of patients treated with placebo. In an 8-week trial, the incidence of ALT or AST elevations ≥ 3 times the upper limit of normal was 13% in patients receiving an intermediate daily dosage or the maximum recommended daily dosage of fenofibrate and was 0% in those receiving the lowest recommended daily dosage of fenofibrate or placebo [see Warnings and Precautions (5.2)].

6.2 Postmarketing Experience

The following adverse reactions have been identified during post-approval use of fenofibrate. Because these reactions are reported voluntarily from a population of uncertain size, it is not always possible to reliably estimate their frequency or establish a causal relationship to drug exposure.

Blood: Anemia, white blood cell decreases

Gastrointestinal: Pancreatitis

General: Asthenia

Hepatobiliary: Increased total bilirubin, hepatitis, cirrhosis

Immune System: Anaphylaxis, angioedema

Lipid Disorders: Severely depressed HDL-cholesterol levels

Musculoskeletal: Myalgia, muscle spasms, rhabdomyolysis, arthralgia

Renal and Urinary: Acute renal failure

Respiratory: Interstitial lung disease

Skin and Subcutaneous Tissue: Photosensitivity reactions, days to months after initiation. This may occur in patients who report a prior photosensitivity reaction to ketoprofen.

7 DRUG INTERACTIONS

Table 2 presents clinically important drug interactions with Antara

Table 2: Clinically Important Drug Interactions with Antara
Statins
Clinical Impact: | Fibrates may cause myopathy when given alone. The risk of myopathy and rhabdomyolysis is increased with concomitant use of fibrates with statins.
Intervention: | Consider if the benefit of using Antara concomitantly with statin therapy outweighs the increased risk of myopathy and rhabdomyolysis. If concomitant use is decided, monitor patients for signs and symptoms of myopathy, particularly during initiation of therapy and during upward dosage titration of statin therapy.
Colchicine
Clinical Impact: | Cases of myopathy and rhabdomyolysis have been reported with concomitant use of colchicine with fenofibrates.
Intervention: | Consider if the benefit of using colchicine concomitantly with Antara outweighs the increased risk of myopathy and rhabdomyolysis. If concomitant use is decided, monitor patients for signs and symptoms of myopathy, particularly during initiation of therapy and during upward dosage titration of colchicine.
Coumarin Anticoagulants
Clinical Impact: | Fibrates may cause potentiation of coumarin-type anticoagulant effects with prolongation of the PT/INR.
Intervention: | Caution should be exercised when coumarin anticoagulants are given in conjunction with Antara. The dosage of the anticoagulants should be reduced to maintain the PT/INR at the desired level to prevent bleeding complications. Frequent PT/INR determinations are advisable until it has been definitely determined that the PT/INR has stabilized
Immunosuppressants
Clinical Impact: | Immunosuppressants such as cyclosporine and tacrolimus can produce nephrotoxicity with decreases in creatinine clearance and rises in serum creatinine, and because renal excretion is the primary elimination route of fibrate drugs including Antara, there is a risk that an interaction will lead to deterioration of renal function.
Intervention: | The benefits and risks of using Antara with immunosuppressants and other potentially nephrotoxic agents should be carefully considered, and the lowest effective dosage employed and renal function monitored.
Bile-Acid Binding Resins
Clinical Impact: | Bile-acid binding resins may bind other drugs given concurrently.
Intervention: | In patients taking a bile acid resin, administer Antara at least 1 hour before or 4 to 6 hours after the bile acid resin to avoid impeding its absorption.

8 USE IN SPECIFIC POPULATIONS

8.1 Pregnancy

Risk Summary

Limited available data with fenofibrate use in pregnant women are insufficient to determine a drug associated risk of major birth defects, miscarriage or adverse maternal or fetal outcomes. In animal reproduction studies, no evidence of embryo-fetal toxicity was observed with oral administration of fenofibrate in rats and rabbits during organogenesis at doses less than or comparable to the maximum recommended clinical dosage of 130 mg of Antara daily, based on body surface area (mg/m^2). Adverse reproductive outcomes occurred at higher doses in the presence of maternal toxicity (see Data). Antara should be used during pregnancy only if the potential benefit justifies the potential risk to the fetus.

The estimated background risk of major birth defects and miscarriage for the indicated population is unknown. In the U.S. general population, the estimated background risk of major birth defects and miscarriage in clinically recognized pregnancies is 2% to 4% and 15% to 20%, respectively.

Data

Animal Data

In pregnant rats given oral dietary doses of 14 mg/kg/day, 127 mg/kg/day, and 361 mg/kg/day from gestation day 6 to 15 during the period of organogenesis, no adverse developmental findings were observed at 14 mg/kg/day (less than the clinical exposure at the maximum recommended human dose [MRHD] of 300 mg fenofibrate daily, comparable to 130 mg Antara daily, based on body surface area comparisons). Increased fetal skeletal malformations were observed at maternally toxic doses (361 mg/kg/day, corresponding to 12 times the clinical exposure at the MRHD) that significantly suppressed maternal body weight gain.

In pregnant rabbits given oral gavage doses of 15 mg/kg/day, 150 mg/kg/day, and 300 mg/kg/day from gestation day 6 to 18 during the period of organogenesis and allowed to deliver, no adverse developmental findings were observed at 15 mg/kg/day (a dose that approximates the clinical exposure at the MRHD, based on body surface area comparisons). Aborted litters were observed at maternally toxic doses (≥ 150 mg/kg/day, corresponding to ≥ 10 times the clinical exposure at the MRHD) that suppressed maternal body weight gain.

In pregnant rats given oral dietary doses of 15 mg/kg/day, 75 mg/kg/day, and 300 mg/kg/day from gestation day 15 through lactation day 21 (weaning), no adverse developmental effects were observed at 15 mg/kg/day (less than the clinical exposure at the MRHD, based on body surface area comparisons), despite maternal toxicity (decreased weight gain). Post-implantation loss was observed at ≥ 75 mg/kg/day (≥ 2 times the clinical exposure at the MRHD) in the presence of maternal toxicity (decreased weight gain). Decreased pup survival was noted at 300 mg/kg/day (10 times the clinical exposure at the MRHD), which was associated with decreased maternal body weight gain/maternal neglect.

8.2 Lactation

Risk Summary

There is no available information on the presence of fenofibrate in human milk, effects of the drug on the breastfed infant, or the effects on milk production. Fenofibrate is present in the milk of rats, and is therefore likely to be present in human milk. Because of the potential for serious adverse reactions in breastfed infants, such as disruption of infant lipid metabolism, women should not breastfeed during treatment with Antara and for 5 days after the final dose.

8.4 Pediatric Use

The safety and effectiveness of Antara have not been established in pediatric patients with severe hypertriglyceridemia or primary hyperlipidemia.

8.5 Geriatric Use

Assess renal function in geriatric patients and follow contraindications and dosing recommendations for patients with renal impairment [see Contraindications (4), Warnings and Precautions (5.3, 5.4), and Use in Specific Populations (8.6)]. While fenofibric acid exposure is not influenced by age, geriatric patients are more likely to have renal impairment, and fenofibric acid is substantially excreted by the kidney [see Clinical Pharmacology (12.3)].

Consider monitoring renal function in geriatric patients taking Antara.

8.6 Renal Impairment

Antara is contraindicated in patients with severe renal impairment (eGFR <30 mL/min/1.73m^2), including those with end-stage renal disease (ESRD) and those receiving dialysis. Dosage reduction is required in patients with mild to moderate renal impairment [see Dosage and Administration (2.4) and Clinical Pharmacology (12.3)]. Patients with severe renal impairment have 2.7-fold higher exposure of fenofibric acid and increased accumulation of fenofibric acid during chronic dosing compared with healthy volunteers. Renal impairment is a risk factor for myopathy and rhabdomyolysis [see Warnings and Precautions (5.3, 5.4), and Clinical Pharmacology (12.3)].

8.7 Hepatic Impairment

The use of Antara has not been evaluated in patients with hepatic impairment. Antara is contraindicated in patients with active liver disease, including those with unexplained persistent liver function abnormalities [see Clinical Pharmacology (12.3)].

10 OVERDOSAGE

In the event of an overdose of Antara, consider contacting the Poison Help line (1-800-222-1222) or a medical toxicologist for additional overdosage management recommendations. There is no specific treatment for overdose with Antara. General supportive care of the patient is indicated, including monitoring of vital signs and observation of clinical status, should an overdose occur. If indicated, elimination of unabsorbed drug should be achieved by emesis or gastric lavage; usual precautions should be observed to maintain the airway. Because fenofibric acid is highly bound to plasma proteins, hemodialysis should not be considered.

11 DESCRIPTION

Antara (fenofibrate) Capsule, is a peroxisome proliferator-activated receptor (PPAR) alpha agonist available as capsules for oral administration. Each capsule contains 43 mg or 130 mg of micronized fenofibrate. The chemical name for fenofibrate is 2-[4-(4-chlorobenzoyl) phenoxy]-2-methyl-propanoic acid, l-methylethyl ester with the following structural formula:

The empirical formula is C20H21O4Cl and the molecular weight is 360.83; fenofibrate is insoluble in water. The melting point is 79 to 82°C. Fenofibrate is a white solid which is stable under ordinary conditions.

Inactive Ingredients: Each gelatin capsule contains sugar spheres, hypromellose, sodium lauryl sulfate, dimethicone, simethicone, and talc. The gelatin capsules also contain black iron oxide, D&C Yellow #10, Indigo carmine FD&C Blue #2, shellac, soya lecithin, sulfur dioxide, titanium dioxide and yellow iron oxide.

12 CLINICAL PHARMACOLOGY

12.1 Mechanism of Action

The active moiety of Antara is fenofibric acid. The pharmacological effects of fenofibric acid in both animals and humans have been studied through oral administration of fenofibrate.

The lipid-modifying effects of fenofibric acid seen in clinical practice have been explained in vivo in transgenic mice and in vitro in human hepatocyte cultures by the activation of PPAR alpha receptor. Through this mechanism, fenofibric acid increases lipolysis and elimination of triglyceride-rich particles from plasma by activating lipoprotein lipase and reducing production of apoprotein C-III (an inhibitor of lipoprotein lipase activity).

12.2 Pharmacodynamics

Fenofibric acid, the active metabolite of fenofibrate, produces reductions in total cholesterol (Total-C), total triglycerides, and triglyceride-rich lipoprotein (VLDL) in treated patients with severe hypertriglyceridemia.

12.3 Pharmacokinetics

Fenofibrate is a pro-drug of the active chemical moiety fenofibric acid. Fenofibrate is converted by ester hydrolysis in the body to fenofibric acid which is the active constituent measurable in the circulation.

Absorption

The absolute bioavailability of fenofibrate cannot be determined as the compound is virtually insoluble in aqueous media suitable for injection. Fenofibrate is insoluble in water and its bioavailability is optimized when taken with meals. However, after fenofibrate is dissolved, fenofibrate is well absorbed from the gastrointestinal tract. Peak plasma levels of fenofibric acid from Antara occur within 4 to 8 hours after administration. There was less than dose-proportional increase in the systemic exposure of fenofibric acid from 43 mg and 130 mg of fenofibrate under fasting conditions.

Doses of three-capsules of 43 mg Antara given concurrently were dose equivalent to single-capsule doses of 130 mg.

Effect of Food:

The extent of absorption of fenofibric acid was unaffected when Antara was taken either in fasted state or with a low-fat meal. However, the Cmax of Antara increased in the presence of a low-fat meal. Tmax was unaffected in the presence of a low-fat meal. In the presence of a high-fat meal, there was a 26% increase in AUC and 108% increase in Cmax of fenofibric acid from Antara relative to fasting state.

Distribution

In healthy volunteers, steady-state plasma levels of fenofibric acid were shown to be achieved within a week of dosing and did not demonstrate accumulation across time following multiple dose administration. Serum protein binding was approximately 99% in normal and hyperlipidemic subjects.

Elimination

Fenofibric acid is eliminated with a half-life of 23 hours, allowing once daily administration of Antara.

Metabolism

Following oral administration, fenofibrate is rapidly hydrolyzed by esterases to the active metabolite, fenofibric acid; no unchanged fenofibrate is detected in plasma. Fenofibric acid is primarily conjugated with glucuronic acid and then excreted in urine. A small amount of fenofibric acid is reduced at the carbonyl moiety to a benzhydrol metabolite which is, in turn, conjugated with glucuronic acid and excreted in urine. In vivo metabolism data indicate that neither fenofibrate nor fenofibric acid undergo oxidative metabolism (e.g., cytochrome P450) to a significant extent.

Excretion

After absorption, fenofibrate is mainly excreted in the urine in the form of metabolites, primarily fenofibric acid and fenofibric acid glucuronide. After administration of radiolabeled fenofibrate, approximately 60% of the dose appeared in the urine and 25% was excreted in the feces.

Specific Populations

Geriatric Patients

In geriatric volunteers 77 to 87 years of age, the apparent oral clearance of fenofibric acid following a single oral dose of fenofibrate was 1.2 L/h, which compares to 1.1 L/h in young adults. This indicates that a similar dosage regimen can be used in geriatric patients with normal renal function, without increasing accumulation of the drug or metabolites [see Dosage and Administration (2.4) and Use in Specific Populations (8.5)].

Pediatric Patients

The Pharmacokinetics of Antara has not been studied in pediatric populations.

Male and Female Patients

No pharmacokinetic difference between males and females has been observed for fenofibrate.

Racial or Ethnic Groups

The influence of race on the pharmacokinetics of fenofibrate has not been studied however fenofibrate is not metabolized by enzymes known for exhibiting inter-ethnic variability.

Patients with Renal Impairment

The pharmacokinetics of fenofibric acid were examined in patients with mild, moderate and severe renal impairment. Patients with severe renal impairment (creatinine clearance [CrCl ≤ 30 mL/min] or estimated glomerular filtration rate [eGFR] < 30 mL/min/1.73m^2) showed a 2.7-fold increase in exposure for fenofibric acid and increased accumulation of fenofibric acid during chronic dosing compared to that of healthy subjects. Patients with mild to moderate renal impairment (CrCl 30 mL/min to 80 mL/min or eGFR 30 to 59 mL/min/1.73m^2) had similar exposure but an increase in the half-life for fenofibric acid compared to that of healthy subjects. Based on these findings, the use of Antara is contraindicated in patients with severe renal impairment, including end-stage renal disease (ESRD) or those receiving dialysis. Dose reduction is required in patients having mild to moderate renal impairment [see Dosage and Administration (2.4)].

Patients with Hepatic Impairment

No pharmacokinetic studies have been conducted in patients with hepatic impairment.

Drug Interaction Studies

In vitro studies using human liver microsomes indicate that fenofibrate and fenofibric acid are not inhibitors of cytochrome (CYP) P450 isoforms CYP3A4, CYP2D6, CYP2E1, or CYP1A2. They are weak inhibitors of CYP2C8, CYP2C19 and CYP2A6, and mild to moderate inhibitors of CYP2C9 at therapeutic concentrations.

Table 3 describes the effects of co-administered drugs on fenofibric acid systemic exposure.

Table 4 describes the effects of co-administered fenofibrate or fenofibric acid on systemic exposure of other drugs.

Table 3: Effects of Co-Administered Drugs on Fenofibric Acid Systemic Exposure from Fenofibrate Administration
Co-Administered Drug | Dosage Regimen of Co-Administered Drug | Dosage Regimen of Fenofibrate | Changes in Fenofibric Acid Exposure
 |  |  | AUC | Cmax
Lipid-lowering medications
Atorvastatin | 20 mg once daily for 10 days | Fenofibrate 160 mg^1 once daily for 10 days | ↓2% | ↓4%
Pravastatin | 40 mg as a single dose | Fenofibrate 3 x 67 mg^2 as a single dose | ↓1% | ↓2%
Fluvastatin | 40 mg as a single dose | Fenofibrate 160 mg^1 as a single dose | ↓2% | ↓10%
Anti-diabetic medications
Glimepiride | 1 mg as a single dose | Fenofibrate 145 mg^1 once daily for 10 days | ↑1% | ↓1%
Metformin | 850 mg three times daily for 10 days | Fenofibrate 54 mg^1 three times daily for 10 days | ↓9% | ↓6%
Rosiglitazone | 8 mg once daily for 5 days | Fenofibrate 145 mg^1 once daily for 14 days | ↑10% | ↑3%
^1TriCor (fenofibrate) oral tablet
^2TriCor (fenofibrate) oral micronized capsule

Table 4: Effects of Fenofibrate Co-Administration on Systemic Exposure of Other Drugs
Dosage Regimen of Fenofibrate | Dosage Regimen of Co-Administered Drug | Changes in Co-Administered Drug Exposure
 |  | Analyte | AUC | Cmax
Lipid-lowering medications
Fenofibrate 160 mg^1 once daily for 10 days | Atorvastatin, 20 mg once daily for 10 days | Atorvastatin | ↓17% | 0%
Fenofibrate 3 x 67 mg^2 as a single dose | Pravastatin, 40 mg as a single dose | Pravastatin | ↑13% | ↑13%
 |  | 3α-Hydroxyl-iso-pravastatin | ↑26% | ↑29%
Fenofibrate 160 mg^1 as a single dose | Fluvastatin, 40 mg as a single dose | (+)-3R, 5S-Fluvastatin | ↑15% | ↑16%
Anti-diabetic medications
Fenofibrate 145 mg^1 once daily for 10 days | Glimepiride, 1 mg as a single dose | Glimepiride | ↑35% | ↑18%
Fenofibrate 54 mg^1 three times daily for 10 days | Metformin, 850 mg three times daily for 10 days | Metformin | ↑3% | ↑6%
Fenofibrate 145 mg^1 once daily for 14 days | Rosiglitazone, 8 mg once daily for 5 days | Rosiglitazone | ↑6% | ↓1%
^1TriCor (fenofibrate) oral tablet
^2TriCor (fenofibrate) oral micronized capsule

13 NONCLINICAL TOXICOLOGY

13.1 Carcinogenesis, Mutagenesis, Impairment of Fertility

Carcinogenesis: Two dietary carcinogenicity studies have been conducted in rats with fenofibrate. In the first 24-month study, Wistar rats were dosed with fenofibrate at 10 mg/kg/day, 45 mg/kg/day, and 200 mg/kg/day, approximately 0.3 times, 1 time, and 6 times the maximum recommended human dose (MRHD), based on body surface area comparisons (mg/m^2). At a dose of 200 mg/kg/day (at 6 times the MRHD), the incidence of liver carcinomas was significantly increased in both sexes. A statistically significant increase in pancreatic carcinomas was observed in males at 1 and 6 times the MRHD; an increase in pancreatic adenomas and benign testicular interstitial cell tumors was observed at 6 times the MRHD in males. In a second 24-month study in a different strain of rats (Sprague-Dawley), doses of 10 mg/kg/day and 60 mg/kg/day (0.3 and 2 times the MRHD) produced significant increases in the incidence of pancreatic acinar adenomas in both sexes and increases in testicular interstitial cell tumors in males at 2 times the MRHD.

A 117-week carcinogenicity study was conducted in rats comparing three drugs: fenofibrate 10 mg/kg/day and 60 mg/kg/day (0.3 and 2 times the MRHD), clofibrate (400 mg/kg/day; 2 times the human dose), and gemfibrozil (250 mg/kg/day; 2 times the human dose) based on mg/m^2 surface area. Fenofibrate increased pancreatic acinar adenomas in both sexes. Clofibrate increased hepatocellular carcinoma and pancreatic acinar adenomas in males and hepatic neoplastic nodules in females. Gemfibrozil increased hepatic neoplastic nodules in males and females, while all three drugs increased testicular interstitial cell tumors in males.

In a 21-month study in CF-1 mice, fenofibrate 10 mg/kg/day, 45 mg/kg/day, and 200 mg/kg/day (approximately 0.2 times, 1 time, and 3 times the MRHD on the basis of mg/m^2 surface area) significantly increased the liver carcinomas in both sexes at 3 times the MRHD. In a second 18-month study at 10 mg/kg/day, 60 mg/kg/day, and 200 mg/kg/day, fenofibrate significantly increased the liver carcinomas in male mice and liver adenomas in female mice at 3 times the MRHD.

Electron microscopy studies have demonstrated peroxisomal proliferation following fenofibrate administration to the rat. An adequate study to test for peroxisome proliferation in humans has not been done, but changes in peroxisome morphology and numbers have been observed in humans after treatment with other members of the fibrate class when liver biopsies were compared before and after treatment in the same individual.

Mutagenesis: Fenofibrate has been demonstrated to be devoid of mutagenic potential in the following tests: Ames, mouse lymphoma, chromosomal aberration and unscheduled DNA synthesis in primary rat hepatocytes.

Impairment of Fertility: In fertility studies rats were given oral dietary doses of fenofibrate, males received 61 days prior to mating and females 15 days prior to mating through weaning which resulted in no adverse effect on fertility at doses up to 300 mg/kg/day (approximately 10 times the MRHD, based on mg/m^2 surface area comparisons).

14 CLINICAL STUDIES

14.1 Overview of Clinical Trials

The effectiveness of Antara has been established in adults with hypertriglyceridemia or primary hyperlipidemia based on adequate and well-controlled trials of other formulations of fenofibrate, referenced below as "fenofibrate." Dosages of fenofibrate used in these trials were comparable to Antara 90 mg per day [see Clinical Pharmacology (12.3)].

14.2 Clinical Trials in Adults with Hypertriglyceridemia

The effects of fenofibrate on serum TG were studied in two randomized, double-blind, placebo-controlled clinical trials of 147 patients with hypertriglyceridemia. Patients were treated for 8 weeks under protocols that differed only in that one entered patients with baseline TG levels of 500 to 1,500 mg/dL, and the other TG levels of 350 to 499 mg/dL. In patients with hypertriglyceridemia and normal cholesterolemia with or without hyperchylomicronemia, treatment with fenofibrate decreased primarily very low density lipoprotein (VLDL), TG and VLDL cholesterol (VLDL-C). Treatment of patients with elevated TG often results in an increase of LDL-C (see Table 5).

Table 5: Effects of Antara in Patients With Hypertriglyceridemia
Trial 1 | Placebo |  |  |  | Antara
Baseline TG Levels 350 to 499 mg/dL | N | Baseline Mean (mg/dL) | Endpoint Mean (mg/dL) | Mean % Change | N | Baseline Mean (mg/dL) | Endpoint Mean (mg/dL) | Mean % Change
TG | 28 | 449 | 450 | -0.5 | 27 | 432 | 223 | -46.2 *
VLDL-TG | 19 | 367 | 350 | 2.7 | 19 | 350 | 178 | -44.1 *
Total-C | 28 | 255 | 261 | 2.8 | 27 | 252 | 227 | -9.1 *
HDL-C | 28 | 35 | 36 | 4 | 27 | 34 | 40 | 19.6 *
LDL-C | 28 | 120 | 129 | 12 | 27 | 128 | 137 | 14.5
VLDL-C | 27 | 99 | 99 | 5.8 | 27 | 92 | 46 | -44.7 *
Trial 2 | Placebo |  |  |  | Antara
Baseline TG levels 500 to 1500 mg/dL | N | Baseline Mean (mg/dL) | Endpoint Mean (mg/dL) | Mean % Change | N | Baseline Mean (mg/dL) | Endpoint Mean (mg/dL) | Mean % Change
TG | 44 | 710 | 750 | 7.2 | 48 | 726 | 308 | -54.5 *
VLDL-TG | 29 | 537 | 571 | 18.7 | 33 | 543 | 205 | -50.6 *
Total-C | 44 | 272 | 271 | 0.4 | 48 | 261 | 223 | -13.8 *
HDL-C | 44 | 27 | 28 | 5.0 | 48 | 30 | 36 | 22.9 *
LDL-C | 42 | 100 | 90 | -4.2 | 45 | 103 | 131 | 45.0*
VLDL-C | 42 | 137 | 142 | 11.0 | 45 | 126 | 54 | -49.4 *
*p < 0.05 vs. placebo

The effect of Antara on serum triglycerides was studied in a double-blind, randomized, 3 arm parallel-group trial of 146 patients. The study population was comprised of 61% male and 39% female patients. Approximately 70% of patients had hypertension and 32% had diabetes. Patients were treated for eight weeks with either a formulation of Antara comparable to 130 mg taken once daily with meals, a formulation of Antara comparable to 130 mg taken once daily between meals, or placebo. Antara 130 mg, whether taken with meals or between meals, had comparable effects on TG and all lipid parameters (See Table 6).

Table 6: Antara Treatment in Patients with Hypertriglyceridemia
 | Placebo (n =50) |  | Antara with meals (n=54) |  | Antara between meals (n=42)
 | Baseline mg/dL (mean) | % Change at endpoint (mean) | Baseline mg/dL (mean) | % Change at endpoint (mean) | Baseline mg/dL (mean) | % Change at endpoint (mean)
Triglycerides | 479 | +0.7 | 475 | -36.7 * | 487 | -36.6 *
Total Cholesterol | 237 | -0.8 | 248 | -5.1 | 241 | -3.4
HDL Cholesterol | 35 | +0.8 | 36 | +13.7 * | 36 | +14.3 *
Non-HDL Cholesterol | 202 | -1.1 | 212 | -8.2 ** | 205 | -6.6 **
LDL Cholesterol | 115 | +3.2 | 120 | +15.4 * | 122 | +14.5
VLDL Cholesterol | 87 | -1.6 | 92 | -34.4 * | 83 | -30.4 *
* p ≤ 0.05 vs placebo
** p ≤ 0.05 vs placebo (log transformed data)

14.3 Clinical Trials in Adults with Primary Hyperlipidemia

The effects of fenofibrate were assessed in four randomized, placebo-controlled, double-blind, parallel group trials in patients with hyperlipidemia and mixed dyslipidemia. Antara therapy reduced LDL-C, Total-C, and TG, and increased HDL-C (see Table 7).

Table 7: Mean Percent Change in Lipid Parameters at End of Treatment†
Treatment Group | Total-C | LDL-C | HDL-C | TG
Mean baseline lipid values (n=646) | 306.9 mg/dL | 213.8 mg/dL | 52.3 mg/dL | 191.0 mg/dL
All fenofibrate (n=361) | -18.7% * | -20.6% * | +11.0% * | -28.9% *
Placebo (n=285) | -0.4% | -2.2% | +0.7% | +7.7%
† Duration of study treatment was 3 to 6 months.
* p=<0.05 vs. Placebo

14.4 Lack of Efficacy in Cardiovascular Outcomes Trials

Fenofibrate did not reduce cardiovascular disease morbidity or mortality in two large, randomized controlled trials of patients with type 2 diabetes mellitus.

The Action to Control Cardiovascular Risk in Diabetes Lipid (ACCORD Lipid) (NCT00000620) trial was a randomized placebo-controlled trial of 5,518 patients (2,765 assigned to receive fenofibrate) with type 2 diabetes mellitus on background statin therapy treated with fenofibrate. The mean age at baseline was 62 years and 31% were female. Overall, 68% were White, 15% were Black or African American; 7% identified as Hispanic or Latino ethnicity. The mean duration of follow-up was 4.7 years. The primary outcome of major adverse cardiovascular events (MACE), a composite of non-fatal myocardial infarction, non-fatal stroke, and cardiovascular disease death was a HR of 0.92 (95% CI, 0.79 to 1.08) for fenofibrate plus statin combination therapy as compared to statin monotherapy.

The Fenofibrate Intervention and Event Lowering in Diabetes (FIELD) trial was a 5-year randomized, placebo controlled trial of 9,795 patients (4,895 assigned to receive fenofibrate) with type 2 diabetes mellitus treated with fenofibrate. The mean age at baseline was 62 years, 37% were female, and 93% were White. The primary outcome of coronary heart disease events was a HR of 0.89 (95% CI, 0.75 to 1.05) with fenofibrate compared to placebo. The HR for total and coronary heart disease mortality, respectively, was 1.11 (95% CI, 0.95 to 1.29) and 1.19 (95% CI, 0.90 to 1.57) with fenofibrate as compared to placebo.

Because of chemical, pharmacological, and clinical similarities between fenofibrate and pemafibrate, findings in a large randomized, placebo-controlled clinical trial with pemafibrate are relevant for Antara.

Pemafibrate did not reduce cardiovascular disease morbidity or mortality in a large, randomized, placebo controlled trial of patients with type 2 diabetes mellitus (TG levels of 200 to 499 mg per deciliter and HDL-C levels of 40 mg per deciliter or lower), on background statin therapy (NCT03071692). The trial was a randomized placebo-controlled trial of 10,497 patients (5,240 assigned to receive pemafibrate) with type 2 diabetes mellitus on background lipid-lowering therapy. The median age at baseline was 64 years and 28% were female. Overall, 86% were White, 5% were Asian, 3% were Black or African American; 19% identified as Hispanic or Latino ethnicity. The median duration of follow-up was 3.4 years. The primary outcome of major adverse cardiovascular events (MACE), a composite of non-fatal myocardial infarction, non-fatal ischemic stroke, coronary revascularization, and death from cardiovascular causes, was a HR of 1.03, (95% CI, 0.91 to 1.15) for pemafibrate plus statin combination therapy as compared to statin monotherapy.

16 HOW SUPPLIED/STORAGE AND HANDLING

Antara capsules are supplied as follows:

Strength | Description | NDC | Package Size (capsules per bottle)
43 mg | Imprinted with "43" and a segmented band, on the light green cap and "ANTARA" and "LUPIN" on the white to off-white body, available in bottles of 30. | NDC 27437 - 109 – 06 | 30
130 mg | Imprinted with "130" and a segmented band, on the dark green cap and "ANTARA" and "LUPIN" on the white body, available in bottles of 30. | NDC 27437 - 110 - 06 | 30
130 mg | Imprinted with "130" and a segmented band, on the dark green cap and "ANTARA" and "LUPIN" on the white body, available in bottles of 30. | NDC 27437 - 110 - 01 | 100

Storage

Store at 25°C (77°F); excursions permitted to 15 to 30°C (59 to 86°F) [See USP Controlled Room Temperature] in a tightly closed container.

17 PATIENT COUNSELING INFORMATION

Hepatotoxicity

Inform patients that Antara may cause liver enzyme elevations and possibly liver failure. Advise patients to promptly report fatigue, anorexia, right upper abdominal discomfort, dark urine or jaundice [see Contraindications (4) and Warnings and Precautions (5.2)].

Myopathy and Rhabdomyolysis

Advise patients that Antara may cause myopathy and rhabdomyolysis. Inform patients that the risk is also increased when taking certain types of medication and they should discuss all medication, both prescription and over the counter, with their healthcare provider. Instruct patients to inform other healthcare providers prescribing a new medication or increasing the dosage of an existing medication that they are taking Antara. Instruct patients to promptly report any unexplained muscle pain, tenderness, or weakness particularly if accompanied by malaise or fever [see Warnings and Precautions (5.3) and Drug Interactions (7)].

Increased Bleeding Risk with Coumarin Anticoagulants

Inform patients that the concomitant use of Antara with coumarin-type anticoagulants may increase the risk of bleeding. Advise patients if they are taking or planning to take coumarin-type anticoagulants to inform their healthcare providers and that increased monitoring may be necessary [see Warnings and Precautions (5.6) and Drug Interactions (7)].

Hypersensitivity Reactions

Inform patients that serious hypersensitivity reactions, such as anaphylaxis and angioedema, have been reported with fenofibrates. Advise patients to report immediately any signs or symptoms suggesting allergic reaction, and to discontinue drug until they have consulted prescribing physicians [see Warnings and Precautions (5.9)].

Pregnancy

Advise patients to inform their healthcare provider of a known or suspected pregnancy to discuss if Antara should be discontinued [see Use in Specific Populations (8.1)].

Lactation

Advise patients that breastfeeding during treatment with Antara is not recommended [see Use in Specific Populations (8.2)].

Missed Doses

If a dose is missed, advise patients to not take an extra dose and to resume treatment with the next dose.

Distributed by:

Lupin Pharmaceuticals, Inc.

Naples, FL 34108

United States

For medical inquiries, call Lupin Pharmaceuticals, Inc. at 1-800-399-2561.

PACKAGE LABEL.PRINCIPAL DISPLAY PANEL

NDA 27437-109-06

ANTARA®

(fenofibrate) capsules

43 mg

Rx only

30 capsules

Lupin Pharmaceuticals Inc.

NDA 27437-110-06

ANTARA®

(fenofibrate) capsules

130 mg

Rx only

30 capsules

Lupin Pharmaceuticals Inc.